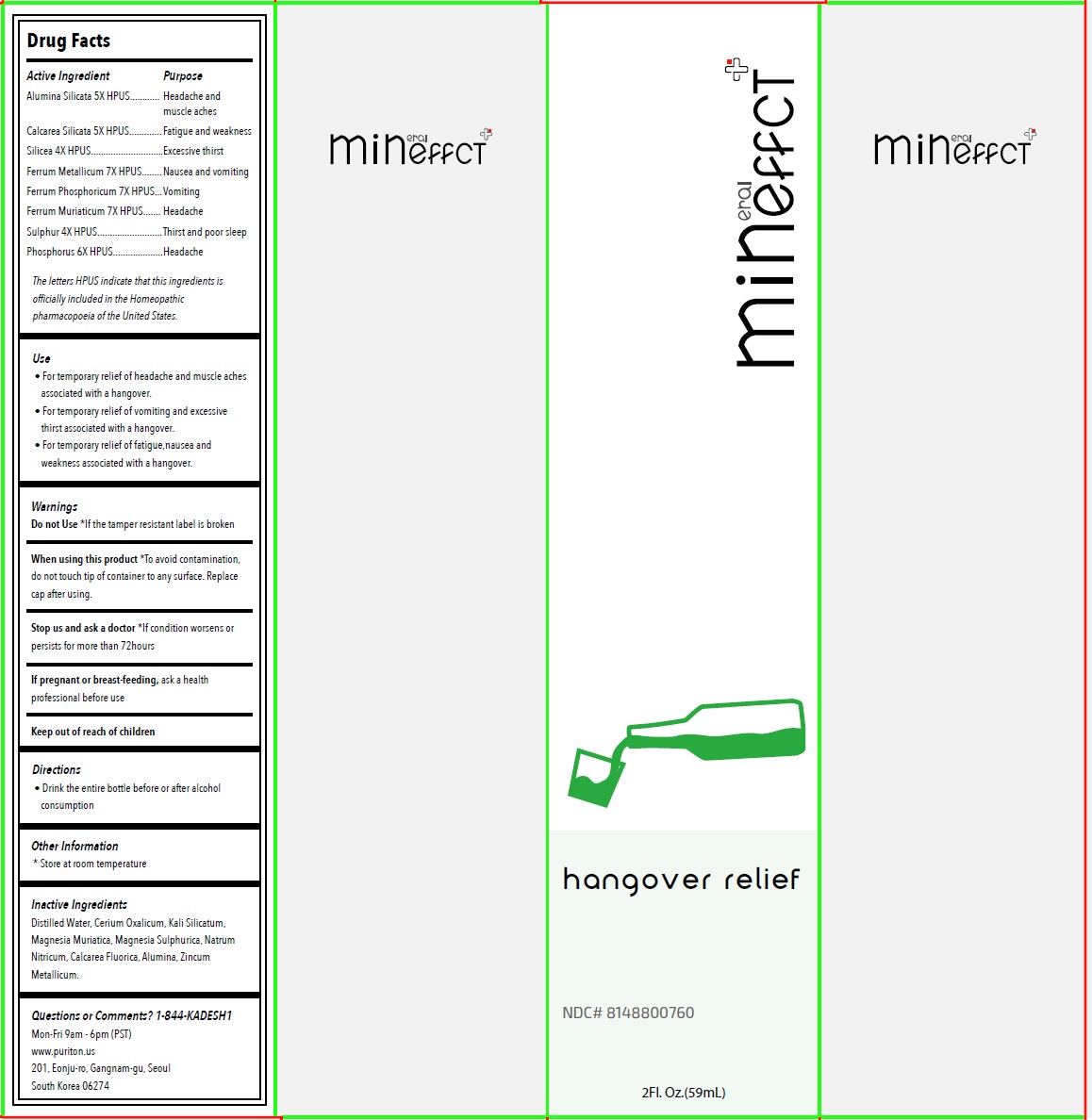 DRUG LABEL: Mineffect hangover relief
NDC: 81488-007 | Form: LIQUID
Manufacturer: Kadesh Incoporation Co,Ltd
Category: homeopathic | Type: HUMAN OTC DRUG LABEL
Date: 20231031

ACTIVE INGREDIENTS: KAOLIN 5 [hp_X]/59 mL; CALCIUM SILICATE 5 [hp_X]/59 mL; SILICON DIOXIDE 4 [hp_X]/59 mL; IRON 7 [hp_X]/59 mL; FERROSOFERRIC PHOSPHATE 7 [hp_X]/59 mL; FERRIC CHLORIDE HEXAHYDRATE 7 [hp_X]/59 mL; SULFUR 4 [hp_X]/59 mL; PHOSPHORUS 6 [hp_X]/59 mL
INACTIVE INGREDIENTS: WATER; CEROUS OXALATE NONAHYDRATE; POTASSIUM SILICATE; MAGNESIUM CHLORIDE; MAGNESIUM SULFATE HEPTAHYDRATE; SODIUM NITRATE; CALCIUM FLUORIDE; ALUMINUM OXIDE; ZINC

Mineffect hangover relief

Active Ingredient

Alumina Silicata 5X HPUS
Calcarea Silicata 5X HPUS
Silicea 4X HPUS
Ferrum Metallicum 7X HPUS
Ferrum Phosphoricum 7X HPUS
Ferrum Muriaticum 7X HPUS
Sulphur 4X HPUS
Phosphorus 6X HPUS

The letters HPUS indicate that this ingredients is officially included in the Homeopathic pharmacopoeia of the United States.

Purpose

Headache and muscle aches
Fatigue and weakness
Excessive thirst
Nausea and vomiting
Vomiting
Headache
Thirst and poor sleep
Headache

Use

• For temporary relief of headache and muscle aches associated with a hangover.
• For temporary relief of vomiting and excessive thirst associated with a hangover.
• For temporary relief of fatigue,nausea and weakness associated with a hangover.

Warnings

Do not Use*If the tamper resistant label is broken

When using this product*To avoid contamination, do not touch tip of container to any surface. Replace cap after using.

Stop us and ask a doctor*If condition worsens or persists for more than 72hours

If pregnant or breast-feeding, ask a health professional before use

Keep out of reach of children

Directions

• Drink the entire bottle before or after alcohol consumption

Other Information

* Store at room temperature

Inactive Ingredients

Distilled Water, Cerium Oxalicum, Kali Silicatum, Magnesia Muriatica, Magnesia Sulphurica, Natrum Nitricum, Calcarea Fluorica, Alumina, Zincum Metallicum.

Questions or Comments? 1-844-KADESH1

Mon-Fri 9am - 6pm (PST)
www.puriton.us
201, Eonju-ro, Gangnam-gu, Seoul
South Korea 06274

mineffCT